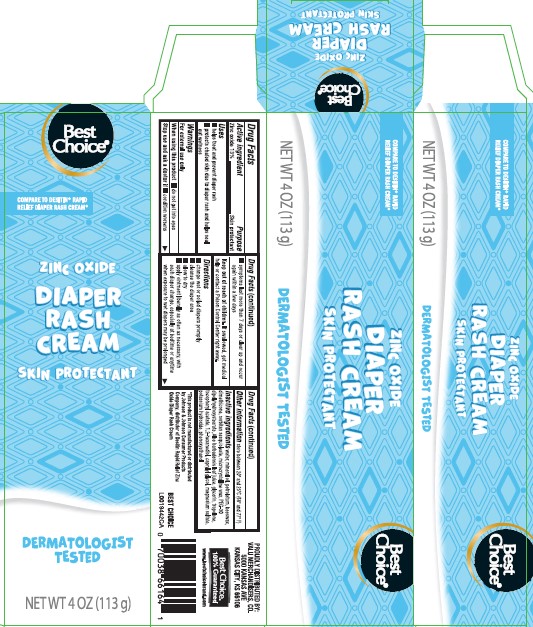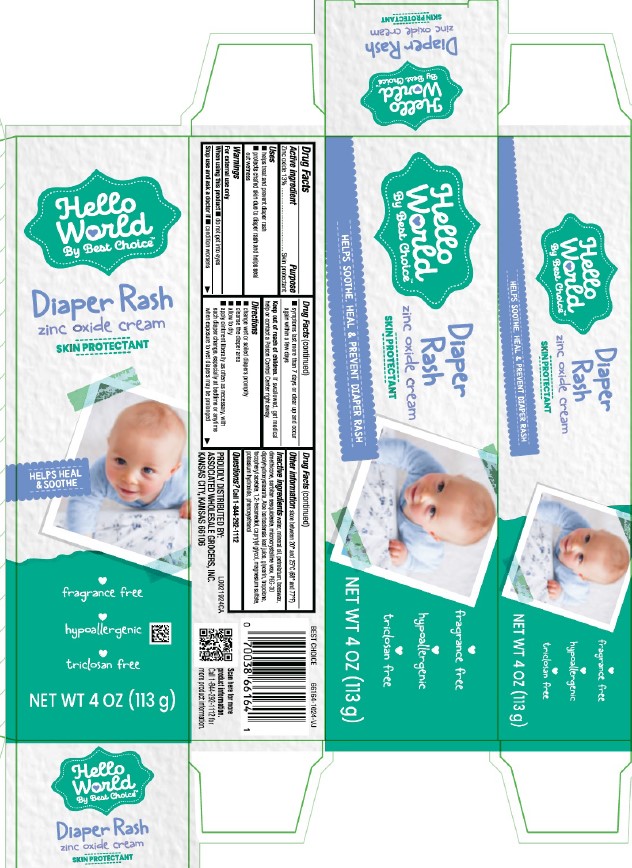 DRUG LABEL: Diaper Rash
NDC: 63941-226 | Form: CREAM
Manufacturer: Valu Merchandisers Company
Category: otc | Type: HUMAN OTC DRUG LABEL
Date: 20260216

ACTIVE INGREDIENTS: ZINC OXIDE 130 mg/1 g
INACTIVE INGREDIENTS: WATER; MINERAL OIL; PETROLATUM; YELLOW WAX; DIMETHICONE; SORBITAN SESQUIOLEATE; MICROCRYSTALLINE WAX; PEG-30 DIPOLYHYDROXYSTEARATE; ALOE VERA LEAF; GLYCERIN; TROPOLONE; .ALPHA.-TOCOPHEROL ACETATE; 1,2-HEXANEDIOL; CAPRYLYL GLYCOL; MAGNESIUM SULFATE MONOHYDRATE; POTASSIUM HYDROXIDE; PHENOXYETHANOL

Best Choice_Hello World 226.002/226AD
Creamy Diaper Rash Ointment

Active ingredient

Zinc oxide 13%

Purpose

Skin protectant

Uses

- helps treat and prevent diaper rash
- protects chafed skin due to diaper rash and helps seal out wetness

Warnings

For external use only

When using this product

- do not get into eyes

Stop use and ask a doctor if

- condition worsens
- symptoms last more than 7 days or clear up and occur again within a few days

Keep out of reach of children.

If swallowed, get medical help or contact a Poison Control Center right away.

Directions

- change wet and soiled diaper promplty
- cleanse the diaper area
- allow to dry
- apply ointment liberally as often as necessary, with each diaper change, especially at bedtime or anytime when exposure to wet diapers may be prolonged

Other information

store between 20º and 25ºC (68º and 77º F)

Inactive ingredients

water, mineral oil, petrolatum, beeswax, dimethicone, sorbitan sesquioleate, microcrystalline wax, PEG-30 dipolyhydroxystearate, Aloe barbadensis leaf juice, glycerin, tropolone, tocopheryl acetate, 1,2-hexanediol, caprylyl glycol, magnesium sulfate, potassium hydroxide, phenoxyethanol

Questions?

Call 1-844-292-1112

ADVERSE REACTION

PROUDLY DISTRIBUTED BY:

ASSOCIATED WHOLESALE GROCERS, INC.

KANSAS CITY, KANSAS 66106

BEST CHOICE 66164-1024-VJ

Scan here for more product information.

Call 1-844-292-1112 for more product information.

principal display panel

COMPARE TO DESITIN RAPID RELIEF DIAPER RASH CREAM*

Best Choice®

Zinc Oxide

DIAPER RASH CREAM SKIN PROTECTANT

DERMATOLOGITST TESTED

NET WT 4 OZ (113 g)

principal display panel

Hello

World

By Best Choice ™

Diaper Rash

zinc oxide cream

SKIN PROTECTANT

HELPS HEAL & SOOTHE

fragrance free

hypoallergenic

triclosan free

NET WT 4 OZ (113 g)